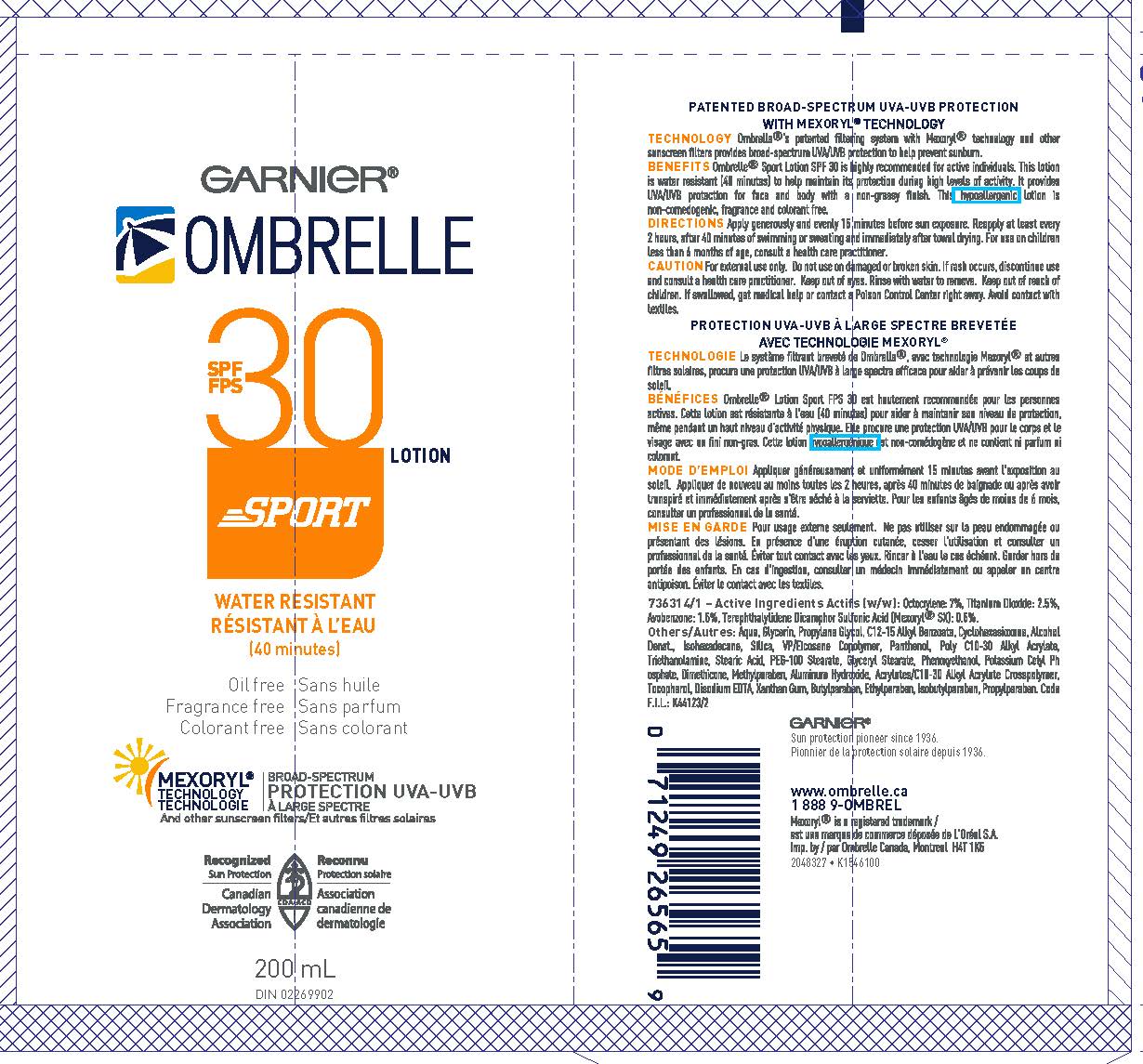 DRUG LABEL: Garnier Ombrelle SPF 30 Sport Water Resistant
NDC: 49967-565 | Form: LOTION
Manufacturer: L'Oreal USA Products Inc
Category: otc | Type: HUMAN OTC DRUG LABEL
Date: 20260107

ACTIVE INGREDIENTS: AVOBENZONE 15 mg/1 mL; OCTOCRYLENE 70 mg/1 mL; ECAMSULE 5 mg/1 mL; TITANIUM DIOXIDE 25 mg/1 mL
INACTIVE INGREDIENTS: WATER; GLYCERIN; PROPYLENE GLYCOL; ALKYL (C12-15) BENZOATE; CYCLOMETHICONE 6; ALCOHOL; ISOHEXADECANE; SILICON DIOXIDE; VINYLPYRROLIDONE/EICOSENE COPOLYMER; PANTHENOL; TROLAMINE; STEARIC ACID; PEG-100 STEARATE; GLYCERYL MONOSTEARATE; PHENOXYETHANOL; POTASSIUM CETYL PHOSPHATE; DIMETHICONE; METHYLPARABEN; ALUMINUM HYDROXIDE; CARBOMER INTERPOLYMER TYPE A (ALLYL SUCROSE CROSSLINKED); TOCOPHEROL; EDETATE DISODIUM; XANTHAN GUM; BUTYLPARABEN; ETHYLPARABEN; ISOBUTYLPARABEN; PROPYLPARABEN

Drug Facts

Active ingredients

Avobenzone 1.5%

Octocrylene 7%

Terephthalylidene Dicamphor Sulfonic Acid 0.5%

Titanium dioxide 2.5%

Warnings

For external use only. Do not use on damaged or broken skin. If rash occurs, discontinue use and consult a health care practitioner. Keep out of eyes. Rinse with water to remove. Keep out of reach of children. If swallowed, get medical help or contact a Poison Control Center right away. Avoid contact with textiles.

Directions

Apply generously and evenly 15 minutes before sun exposure. Reapply at least every 2 hours, after 40 minutes of swimming or sweating and immediately after towel drying. For use on children less than 6 months of age, consult a health care practitioner.

Inactive ingredients

water, glycerin, propylene glycol, C12-15 alkyl benzoate, cyclohexasiloxane, alcohol denat., isohexadecane, silica, VP/eicosene copolymer, panthenol, poly C10-30 alkyl acrylate, triethanolamine, stearic acid, PEG-100 stearate, glyceryl stearate, phenoxyethanol, potassium cetyl phosphate, dimethicone, methylparaben, aluminum hydroxide, acrylates/C10-30 alkyl acrylate crosspolymer, tocopherol, disodium EDTA, xanthan gum, butylparaben, ethylparaben, isobutylparaben, propylparaben